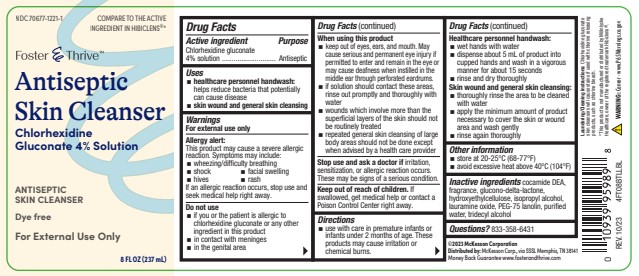 DRUG LABEL: Foster and Thrive
NDC: 70677-1221 | Form: SOLUTION
Manufacturer: McKesson Corporation
Category: otc | Type: HUMAN OTC DRUG LABEL
Date: 20251216

ACTIVE INGREDIENTS: CHLORHEXIDINE GLUCONATE 4 g/100 mL
INACTIVE INGREDIENTS: WATER; ISOPROPYL ALCOHOL; LAURAMINE OXIDE; TRIDECYL ALCOHOL; GLUCONOLACTONE; PEG-75 LANOLIN; COCO DIETHANOLAMIDE; HYDROXYETHYL CELLULOSE (2000 CPS AT 1%)

COMP Foster & Thrive 4% 8oz

Active Ingredient

Chlorhexidine Gluconate 4%

Purpose

Antiseptic

Uses

- healthcare personnel handwash: helps reduce bacteria that potentially can cause disease
- skin wound and general skin cleansing

Warnings

For external use only

Allergy alert:

This product may casue a severe allergic reaction. Symptoms may include:

- wheezing/difficulty breathing
- shock
- facial swelling
- hives
- rash

If an allergic reaction occurs, stop use and seek medical help right away

Do not use

- if you or the patient is allergic to chlorhexidine gluconate or any other ingredient in this product
- in contact with meninges
- in the gential area

When using this product

- keep out of eyes, ears, and mouth. May cause serious and permanent eye injury if permitted to enter and remain in the eye or may cause deafness when instilled in the middle ear through perforated eardrums.
- is solution should contact these areas, rinse out promptly and throughly with water
- wounds which involve more than the superfical layers of the skin should not be routinely treated
- repeated general skin cleansing of large body areas should not be done expect when advised by health care provider

Stop use and ask a doctor if irritation , sensitization, or allergic reaction occurs. There may be signs of a serious condition

Keep out of reach of children. If swallowed, get medical help or contact a Poison Control Center right away

Directions

- use with care in premature infants or infants under 2 months of age. These products may cause irritation or chemical burns.

Healthcare personnel handwash:

- wet hands with water
- dispense about 5 mL of product into cupped hands and wash in vigorous manner for about 15 seconds
- rinse and dry throughly

Skin wound and general skin cleansing:

- throughly rinse the area to be cleaned with water
- apply the minimum amount of product necessary to cover the skin or wound area and wash gently
- rinse again throughly

Other information

- store at 20-25ºC (68-77ºF)
- avoid excessive heat about 40ºC (104ºF)

Inactive ingredients

cocamide DEA, fragrance, glucono-delta-lactone, hydroxyethylcellulose, isopropyl alcohol, lauramine oxide, PEG-75 lanolin, purified water, tridecyl alcohol

Questions?

833-358-6431

Laundering/Cleaning Instructions

Chlorhexidine gluconate skin cleanser will cause stains if used with chlorine releasing products, such as chlorine bleach.

Distribution Statement

*This product is not manufactured or distributed by Molnlycke Healthcare, owner of Hibiclens®

REV. 10/23 4FT08BTLLBL

Prop 65 statement

WARNING: Cancer - www.P65Warnings.co.giv

Distribution Block + Claim

©2023 McKesson Corporation

Distributed by: McKesson Corp., via SSSL, Memphis, TN 38141

Money Back Guarantee www.fosterandthrive.com

Principle Display Panel

NDC 70677-1221-1

Compared to the Active Ingredient in Hibiclens®

Foster & Thrive™

Antiseptic Skin Cleanser

Chlorhexidine Gluconate 4% Solution

Antiseptic Skin Cleanser

Dye Free

For External Use Only

8 FL OZ (237 mL)